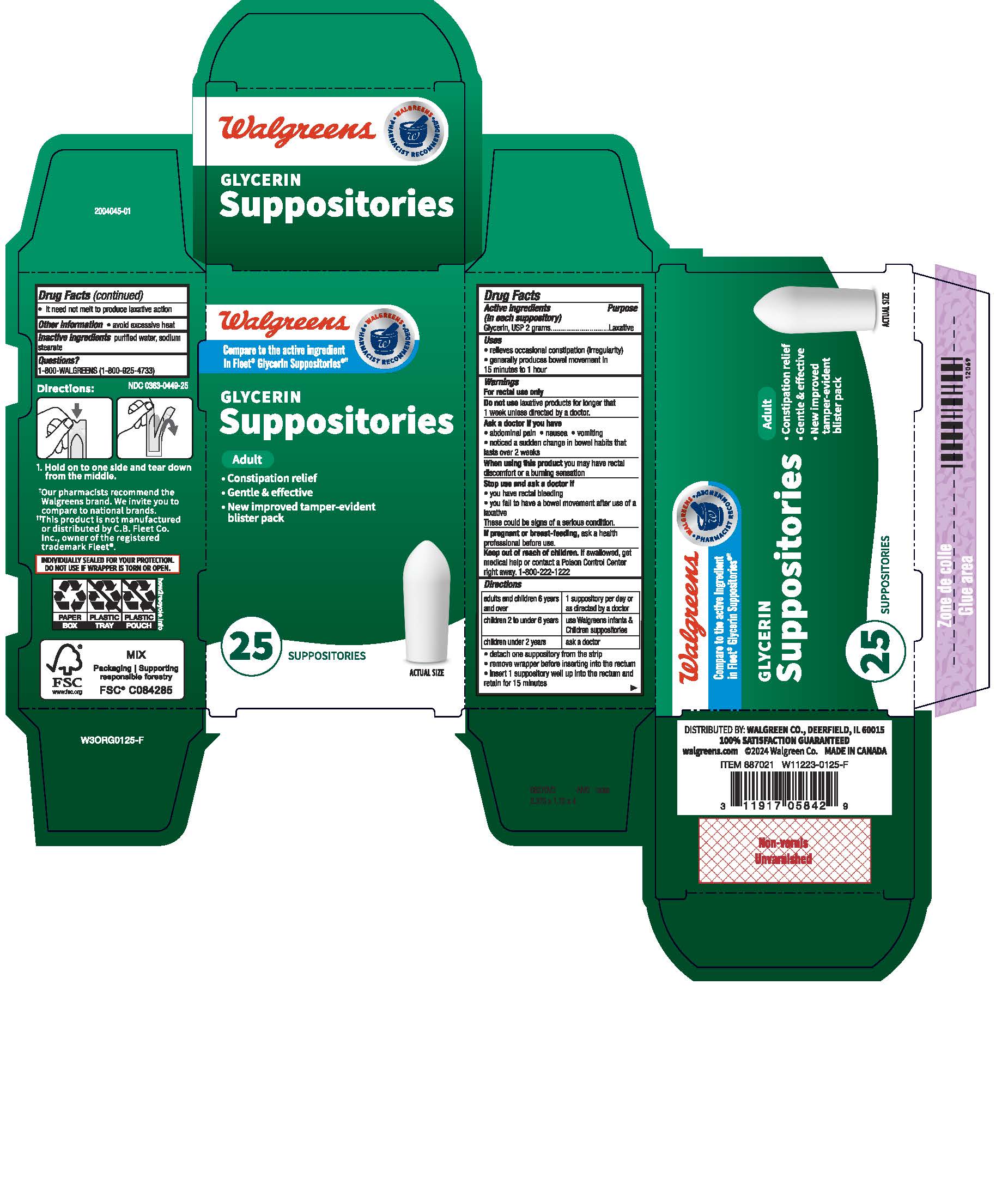 DRUG LABEL: WALGREEN GLYCERIN ADULT
NDC: 0363-0449 | Form: SUPPOSITORY
Manufacturer: Walgreens
Category: otc | Type: HUMAN OTC DRUG LABEL
Date: 20250324

ACTIVE INGREDIENTS: GLYCERIN 1800 mg/1 1
INACTIVE INGREDIENTS: SODIUM HYDROXIDE

WALGREENS GLYCERIN ADULT

ACTIVE INGREDIENT

(in each suppository)
Glycerin, USP 2 grams

Ask a doctor before use if you have
- abdominal pain - nausea - vomiting
- noticed a sudden change in bowel habits that lasts over 2 weeks

Do not use laxative products for longer than 1 week unless directed by a doctor

KEEP OUT OF REACH OF CHILDREN

If swallowed, get medical help or contact a Poison Control Center right away.

PREGNANCY OR BREAST FEEDING

If pregnant or breast-feeding, ask a health professional before use.

Stop use and ask a doctor if you have rectal bleeding or fail to have a bowel movement
after use of a laxative.
These could be signs of a serious condition.

PURPOSE

Laxative

When using this product you may have rectal discomfort or a burning sensation

WARNINGS

For rectal use only

DOSAGE AND ADMINISTRATION

adults and children 6 years of age and over........1 suppository per day or as directed by a doctor
children 2 to under 6 years................................use Walgreens Infants & Children suppositories
children under 2 years.......................................ask a doctor

OTHER SAFETY INFORMATION

-keep tightly closed
-avoid excessive heat

INACTIVE INGREDIENT

purified water, sodium hydroxide, stearic acid

INDICATIONS AND USAGE

-relieves occasional constipation (irregularity)
-generally produces bowel movement in 1/4 to 1 hour